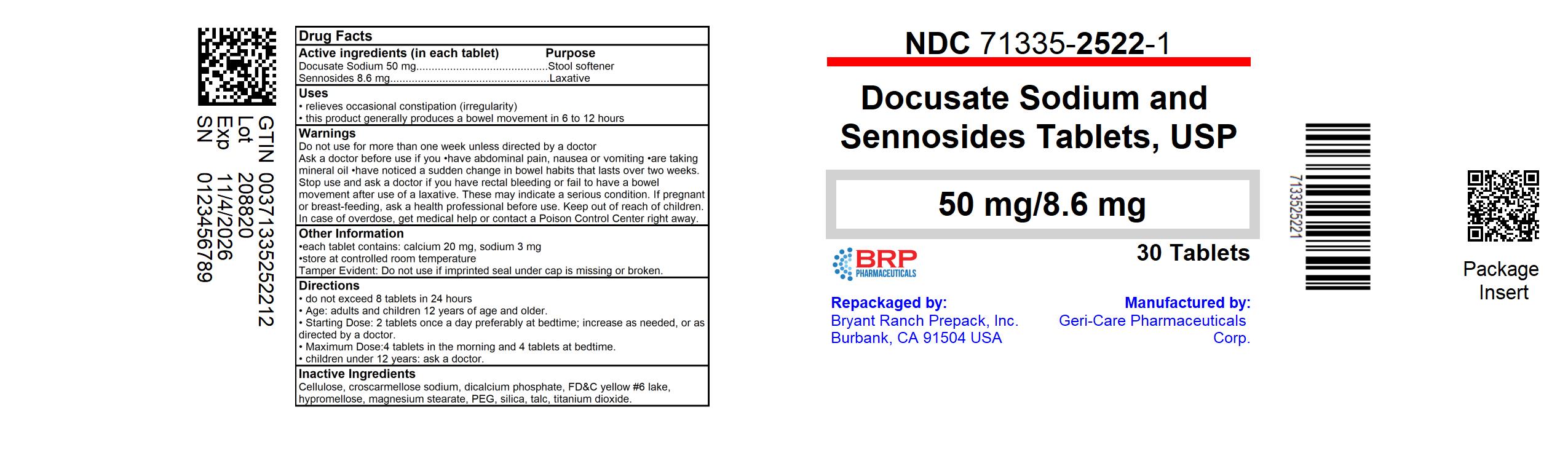 DRUG LABEL: Stool Softener with Laxative
NDC: 71335-2522 | Form: TABLET, FILM COATED
Manufacturer: Bryant Ranch Prepack
Category: otc | Type: HUMAN OTC DRUG LABEL
Date: 20241104

ACTIVE INGREDIENTS: SENNOSIDES 8.6 mg/1 1; DOCUSATE SODIUM 50 mg/1 1
INACTIVE INGREDIENTS: POLYETHYLENE GLYCOL, UNSPECIFIED; HYPROMELLOSE, UNSPECIFIED; FD&C BLUE NO. 2; TITANIUM DIOXIDE; MAGNESIUM STEARATE; MICROCRYSTALLINE CELLULOSE; CROSCARMELLOSE SODIUM; DIBASIC CALCIUM PHOSPHATE DIHYDRATE; FD&C RED NO. 40; SILICON DIOXIDE; TALC

Gericare 303B (304)

Active ingredient (in each tablet)

Docusate Sodium 50 mg
Sennosides 8.6 mg

Purpose

Stool softener

Stimulant laxative

Uses

- relieves occasional constipation (irregularity)

- this product generally produces bowel movement in 6 to 12 hours

Warnings

Do not use

- laxative products for longer than 1 week unless directed by a doctor
- if you are presently taking mineral oil, unless directed by a doctor

Ask a doctor before use if you have

- stomach pain
- nausea
- vomiting
- noticed a sudden change in bowel habits that lasts over 2 weeks

Stop use and ask a doctor if you have rectal bleeding or fail to have a bowel movement after use of a laxative. These could

be signs of a serious condition.

If pregnant or breast-feeding, ask a health professional before use.

Keep out of reach of children. In case of overdose, get medical help or contact a Poison Control Center right away.

Directions

- Take only by mouth. Doses may be taken as a single daily dose, preferably in the evening, or in divided doses

adults and children 12 years and over | take 2-4 tablets daily
children under 12 years of age | ask a doctor

Other information

- each tablet contains: calcium 20 mg, sodium 3 mg
- store at controlled room temperature
- Tamper Evident: Do not use if imprinted seal under cap is missing or broken.
- product of India

Inactive ingredients

cellulose, croscarmellose sodium, dicalcium phosphate, FD&C blue #2 lake, FD&C red #40 lake, hypromellose, magnesium stearate, PEG, silica, talc, titanium dioxide.

HOW SUPPLIED

Stool softener with stimulant laxative each tablet contains docusate sodium 50 mg sennosides 8.6 mg. Red colored, round shaped and the imprint code in PSD21.

NDC: 71335-2522-1: 30 Tablets in a BOTTLE

NDC: 71335-2522-2: 120 Tablets in a BOTTLE

NDC: 71335-2522-3: 60 Tablets in a BOTTLE

NDC: 71335-2522-4: 90 Tablets in a BOTTLE

NDC: 71335-2522-5: 100 Tablets in a BOTTLE

NDC: 71335-2522-6: 28 Tablets in a BOTTLE

NDC: 71335-2522-7: 56 Tablets in a BOTTLE

NDC: 71335-2522-8: 14 Tablets in a BOTTLE

NDC: 71335-2522-9: 20 Tablets in a BOTTLE

Store at controlled room temperature.

Tamper Evident: Do not use if imprinted seal under cap is missing or broken.

Repackaged/Relabeled by:
Bryant Ranch Prepack, Inc.
Burbank, CA 91504

PACKAGE LABEL

Docusate/ Sennosides 50/8.6 mg Tablet